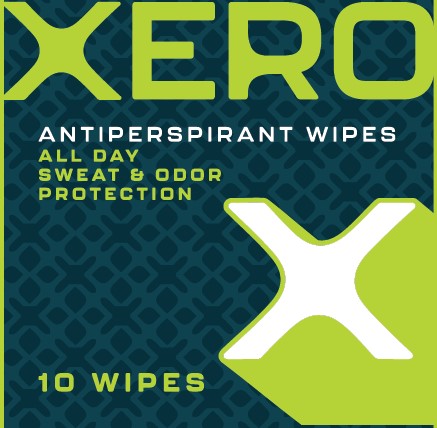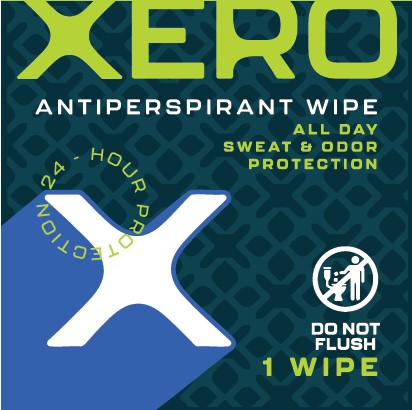 DRUG LABEL: Antiperspirant Wipe
NDC: 85505-395 | Form: CLOTH
Manufacturer: Stock Your Home
Category: otc | Type: HUMAN OTC DRUG LABEL
Date: 20250422

ACTIVE INGREDIENTS: ALUMINUM CHLOROHYDRATE 15 g/100 1
INACTIVE INGREDIENTS: POLYSORBATE 20; PHENOXYETHANOL; WATER; .ALPHA.-TOCOPHEROL ACETATE; TOCOPHEROL; USNEA BARBATA; SORBIC ACID; CHLORPHENESIN; POTASSIUM SORBATE; SAGE; BENZOIC ACID; BENZYL ALCOHOL; PEG-180

XERO Antiperspirant Wipe

Active ingredient

Aluminum Chlorohydrate 15%

Purpose

Antiperspirant

Use

Reduces underarm perspiration

Warnings

For external use only

Do not use

■ on broken or irritation skin

■ immediately after shaving

Ask a doctor before use if you have kidney disease

When using this product ■ do not use in or near eyes ■ apply to underarms only

Stop use and ask a doctor if rash or irritation develops

Keep out of reach of children. If swallowed, get medical help or contact a Poison Control Center right away.

Directions

■ open packet ■ remove and unfold wipe ■ apply to underarm only

Inactive ingredients

benzoic acid, benzyl alcohol, chlorphenesin, fragrance, PEG-180, phenoxyethanol, polysorbate 20, potassium sorbate, salvia officinalis (sage) leaf extract, sorbic acid, tocopherol, tocopheryl acetate, usnea barbata (lichen) extract, water

Principal Display Panel

XERO

ANTIPERSPIRANT WIPES

ALL DAY SWEAT & ODOR

PROTECTION

24- HOER PROTECTION

DO NOT FLUSH

1 WIPE

10 WIPES